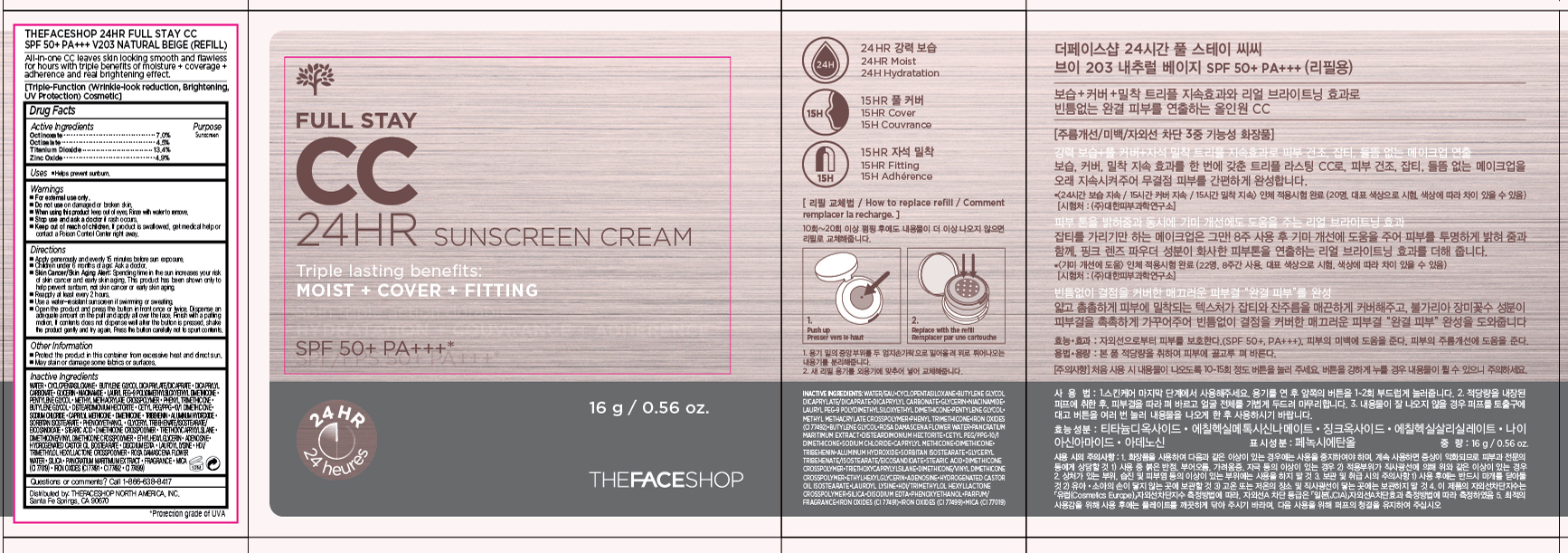 DRUG LABEL: FULL STAY
NDC: 51523-469 | Form: CREAM
Manufacturer: THEFACESHOP CO., LTD.
Category: otc | Type: HUMAN OTC DRUG LABEL
Date: 20150929

ACTIVE INGREDIENTS: OCTINOXATE 1.12 g/16 g; OCTISALATE 0.72 g/16 g; TITANIUM DIOXIDE 2.14 g/16 g; ZINC OXIDE 0.78 g/16 g
INACTIVE INGREDIENTS: WATER

FULL STAY CC 24HR SUNSCREEN CREAM V203 NATURAL BEIGE (REFILL) SPF 50+ PA+++ 34200469

Active Ingredients

Octinoxate 7.0 %
Octisalate 4.5 %
Titanium Dioxide 13.4 %
Zinc Oxide 4.9 %

Purpose

Sunscreen

Sunscreen

Sunscreen

Sunscreen

Uses

Helps prevent sunburn.

Warnings

For external use only.

Do not use on damaged or broken skin

When using this product keep out of eyes. Rinse with water to remove.

Stop use and ask a doctor if rash occurs.

Keep out of reach of children. If product is swallowed, get medical help or contact a Poison Control Center right away.

Directions

Apply generously and evenly 15 minutes before sun exposure.
Children under 6 months of age: Ask a doctor.
Skin Cancer/Skin Aging Alert: Spending time in the sun increases your risk of skin cancer and early skin aging. This product has been shown only to help prevent sunburn, not skin cancer or early skin aging.
Reapply at least every 2 hours.
Use a water-resistant sunscreen if swimming or sweating.

Open the product and press the button in front once or twice. Dispense an adequate amount on the puff and apply all over the face. Finish with a patting motion. If contents does not dispense well after the button is pressed, shake the product gently and try again. Press the button carefully not to spurt contents.

OTHER SAFETY INFORMATION

Protect the product in this container from excessive heat and direct sun.

May stain or damage some fabrics or surfaces.

Inactive Ingredients:

Water, Cyclopentasiloxane, Butylene Glycol Dicaprylate/Dicaprate, Dicaprylyl Carbonate, Glycerin, Niacinamide, Lauryl PEG-9 Polydimethylsiloxyethyl Dimethicone, Pentylene Glycol, Phenyl Trimethicone, Methyl Methacrylate Crosspolymer, Butylene Glycol, Disteardimonium Hectorite, Cetyl PEG/PPG-10/1 Dimethicone, Sodium Chloride, Caprylyl Methicone, Dimethicone, Tribehenin, Aluminum Hydroxide, Sorbitan Isostearate, Phenoxyethanol, Glyceryl Tribehenate/Isostearate/Eicosandioate, Stearic Acid, Triethoxycaprylylsilane, Dimethicone Crosspolymer, Dimethicone/Vinyl Dimethicone Crosspolymer, Ethylhexylglycerin, Adenosine, Hydrogenated Castor Oil Isostearate, Disodium EDTA, Lauroyl Lysine, HDI/Trimethylol Hexyllactone Crosspolymer, Rosa Damascena Flower Water, Silica, Pancratium Maritimum Extract, Fragrance, Mica (CI 77019), Iron Oxides (CI 77491, CI 77492, CI 77499)

Questions or comments? Call 1-866-638-8417

Distributed by:

THEFACESHOP NORTH AMERICA, INC.

Santa Fe Springs, CA 90670

PACKAGE LABEL

FULL STAY CC

24HR SUNSCREEN CREAM

V203 NATURAL BEIGE (REFILL) SPF 50+ PA+++

All-in-one CC leaves skin looking smooth and flawless for hours

with triple benefits of moisture + coverage + adherence and real brightening effect.